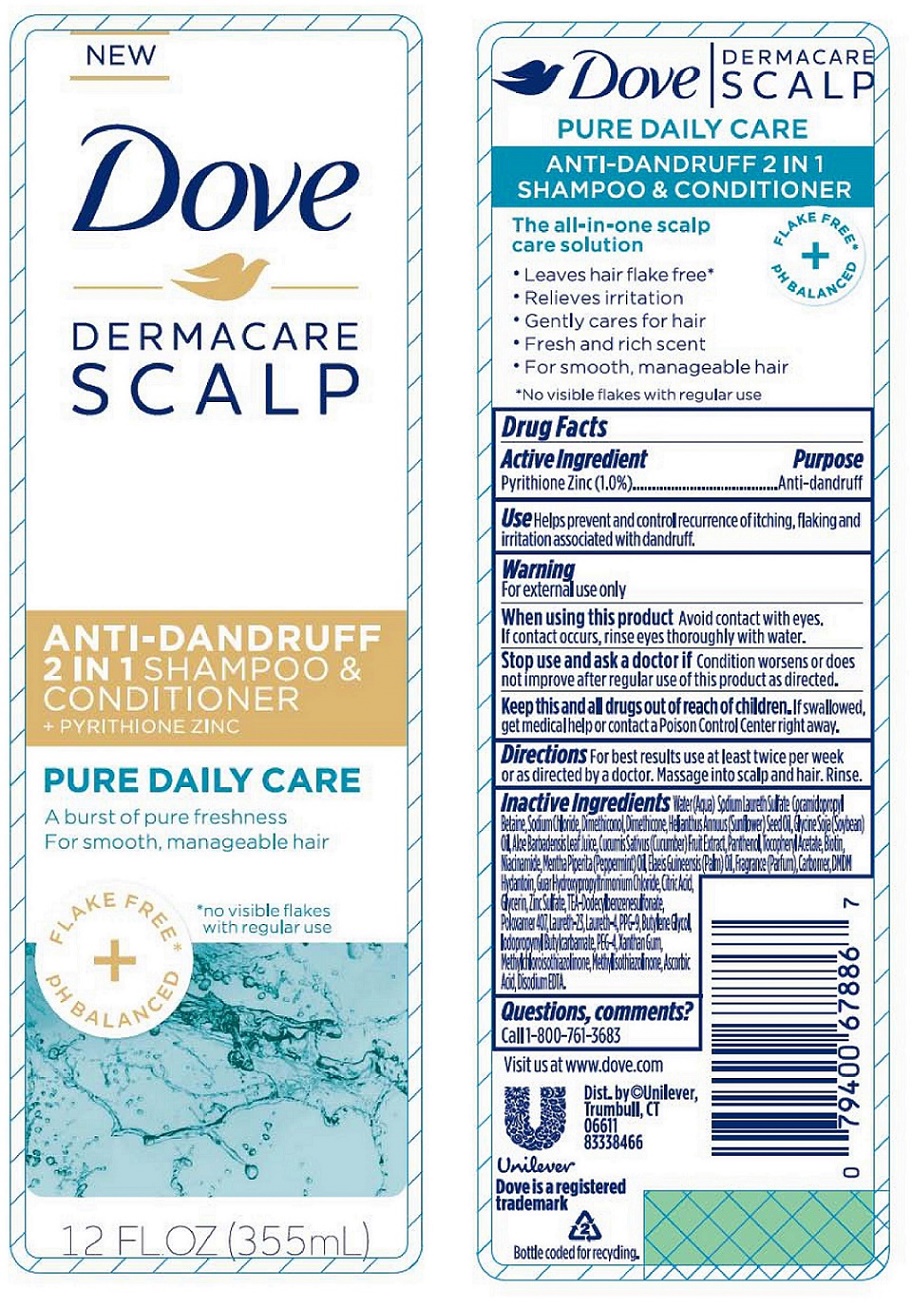 DRUG LABEL: Dove

NDC: 64942-1485 | Form: SHAMPOO
Manufacturer: Conopco, Inc. d/b/a Unilever
Category: otc | Type: HUMAN OTC DRUG LABEL
Date: 20221207

ACTIVE INGREDIENTS: PYRITHIONE ZINC 1 g/100 mL
INACTIVE INGREDIENTS: WATER; SODIUM LAURETH-3 SULFATE; COCAMIDOPROPYL BETAINE; SODIUM CHLORIDE; DIMETHICONOL (40 CST); DIMETHICONE; SUNFLOWER OIL; SOYBEAN OIL; ALOE VERA LEAF; CUCUMBER; PANTHENOL; .ALPHA.-TOCOPHEROL ACETATE, D-; BIOTIN; NIACINAMIDE; PEPPERMINT OIL; PALM OIL; CARBOMER HOMOPOLYMER TYPE C (ALLYL PENTAERYTHRITOL CROSSLINKED); DMDM HYDANTOIN; GUAR HYDROXYPROPYLTRIMONIUM CHLORIDE (1.7 SUBSTITUENTS PER SACCHARIDE); CITRIC ACID MONOHYDRATE; GLYCERIN; ZINC SULFATE, UNSPECIFIED FORM; TRIETHANOLAMINE DODECYLBENZENESULFONATE; POLOXAMER 407; LAURETH-23; LAURETH-4; PPG-9; BUTYLENE GLYCOL; IODOPROPYNYL BUTYLCARBAMATE; POLYETHYLENE GLYCOL 200; XANTHAN GUM; METHYLCHLOROISOTHIAZOLINONE; METHYLISOTHIAZOLINONE; ASCORBIC ACID; EDETATE DISODIUM

Dove Dermacare Scalp Pure Daily Care 2 In 1 Anti-Dandruff Shampoo and Conditioner

Active Ingredient

Pyrithione Zinc (1.0%)

Purpose

Anti-dandruff

Use

Helps prevent and control recurrence of itching, flaking and irritation associated with dandruff.

Warning

For external use only
When using this product Avoid contact with eyes. If contact occurs, rinse eyes thoroughly with water.
Stop use and ask a doctor if Condition worsens or does not improve after regular use of this product as directed.

KEEP OUT OF REACH OF CHILDREN

Keep this and all drugs out of reach of children. If swallowed, get medical help or contact a Poison Control Center right away.

Directions

For best results use at least twice per week or as directed by a doctor. Massage into scalp and hair. Rinse.

Inactive Ingredients

Water(Aqua), Sodium Laureth Sulfate, Cocamidopropyl Betaine, Sodium Chloride, Dimethiconol, Dimethicone, Helianthus Annuus (Sunflower) Seed Oil, Glycine Soja (Soybean) Oil, Aloe Barbadensis Leaf Juice, Cucumis Sativus(Cucumber)Fruit Extract, Panthenol, Tocopheryl Acetate, Biotin, Niacinamide, Mentha Piperita(Peppermint)Oil, Elaeis Guineensis(Palm)Oil, Fragrance (Parfum), Carbomer, DMDM Hydantoin, Guar Hydroxypropyltrimonium Chloride, Citric Acid, Glycerin, Zinc Sulfate, TEA-Dodecylbenzenesulfonate, Poloxamer 407, Laureth-23, Laureth-4, PPG-9, Butylene Glycol, Iodopropynyl Butylcarbamate, PEG-4, Xanthan Gum, Methylchloroisothiazolinone, Methylisothiazolinone, Ascorbic Acid, Disodium EDTA.

Questions, comments?

Call 1-800-761-3683

A burst of pure freshness

FLAKE FREE* + pH BALANCED

The all-in-one scalp care solution

- Leaves hair flake free*
- Relieves irritation
- Gently cares for hair
- Fresh and rich scent
- For smooth, manageable hair

*No visible flakes with regular use